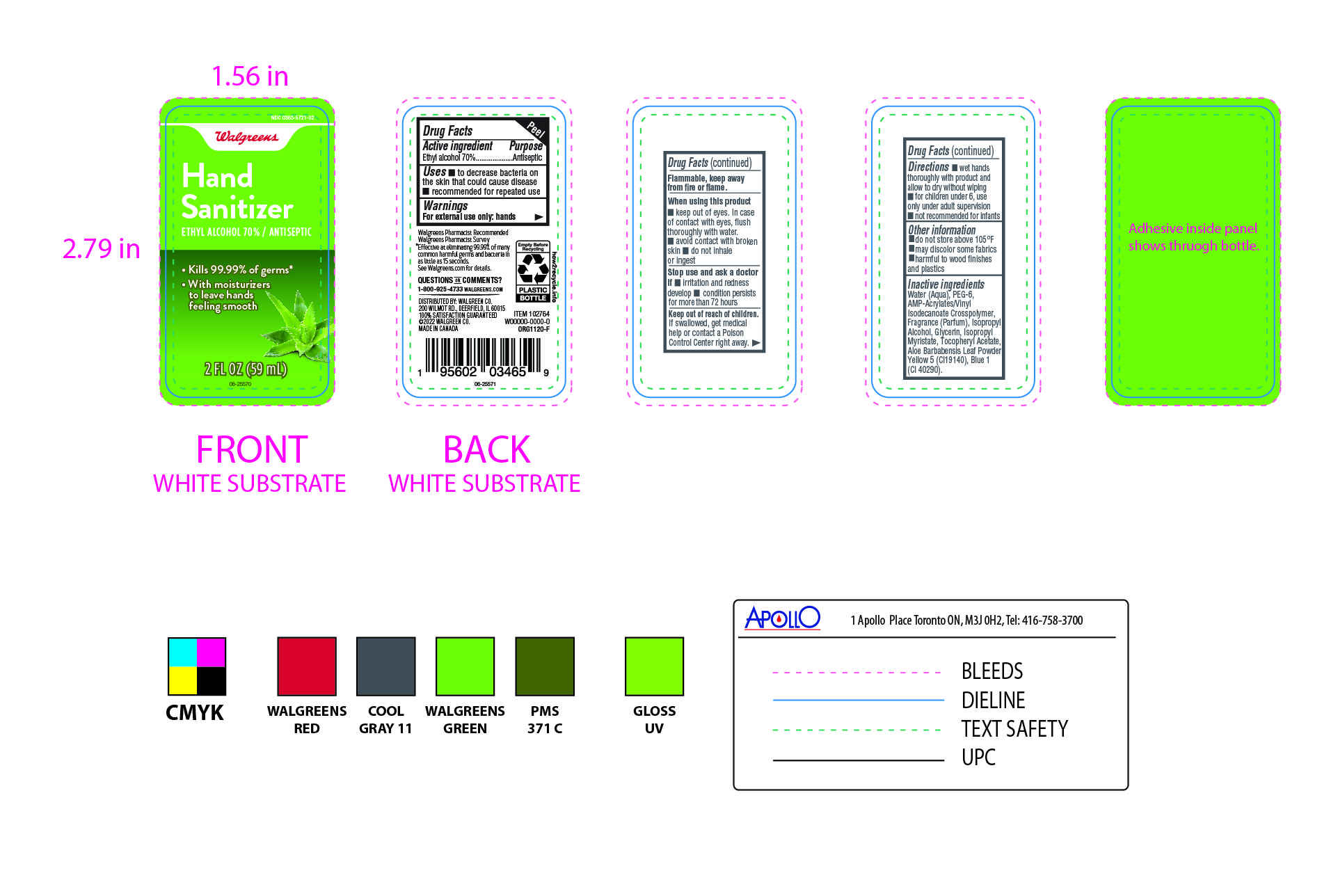 DRUG LABEL: Walgreens
NDC: 0363-5721 | Form: GEL
Manufacturer: walgreens
Category: otc | Type: HUMAN OTC DRUG LABEL
Date: 20250201

ACTIVE INGREDIENTS: ALCOHOL 700 mg/1 mL
INACTIVE INGREDIENTS: FRAGRANCE CLEAN ORC0600327; ISOPROPYL MYRISTATE; YELLOW 5; GLYCERIN; ALOE VERA LEAF; PEG-6; WATER; ISOPROPYL ALCOHOL; .ALPHA.-TOCOPHEROL ACETATE, D-; BLUE 1; ACRYLATES/VINYL ISODECANOATE CROSSPOLYMER (10000 MPA.S NEUTRALIZED AT 0.5%)

0363-5721-02 Walgreens Hand sanitizer

ACTIVE INGREDIENT

Ethyl Alcohol 70%

PURPOSE

Antiseptic

WARNINGS

For External use only : hands

WHEN USING

- keep out of eyes, In case of contact with eyes, flush throughly with water.
- avoid contact with broken skin
- do not inhale or ingest.

ASK DOCTOR

if

- irritation and redness develop
- condition persists for more than 72 hours.

KEEP OUT OF REACH OF CHILDREN

if swallowed , get medical help or contact a poision Control Centre right away.

DOSAGE AND ADMINISTRATION

- wet hands thoroughly with product and allow to dry without wiping .
- for children under 6, use only under adult supervision.
- not recommended for infants

STORAGE AND HANDLING

- do not store above 105F.
- may discolor some fabric
- harmful to wood finishes and plastics

INACTIVE INGREDIENT

Water, PEG-6, AMP-Acrylates/Vinyl Isodecanoate Crosspolymer, Fragrance (Parfum), Isopropyl Alcohol, Glycerin, Isopropyl Myristate, Tocopheryl Acetate, Aloe Barbabensis leaf Powder, Yellow 5, Blue 1

INDICATIONS AND USAGE

- to reduce bacteria on the skin that could cause disease
- recommeded for repeated use